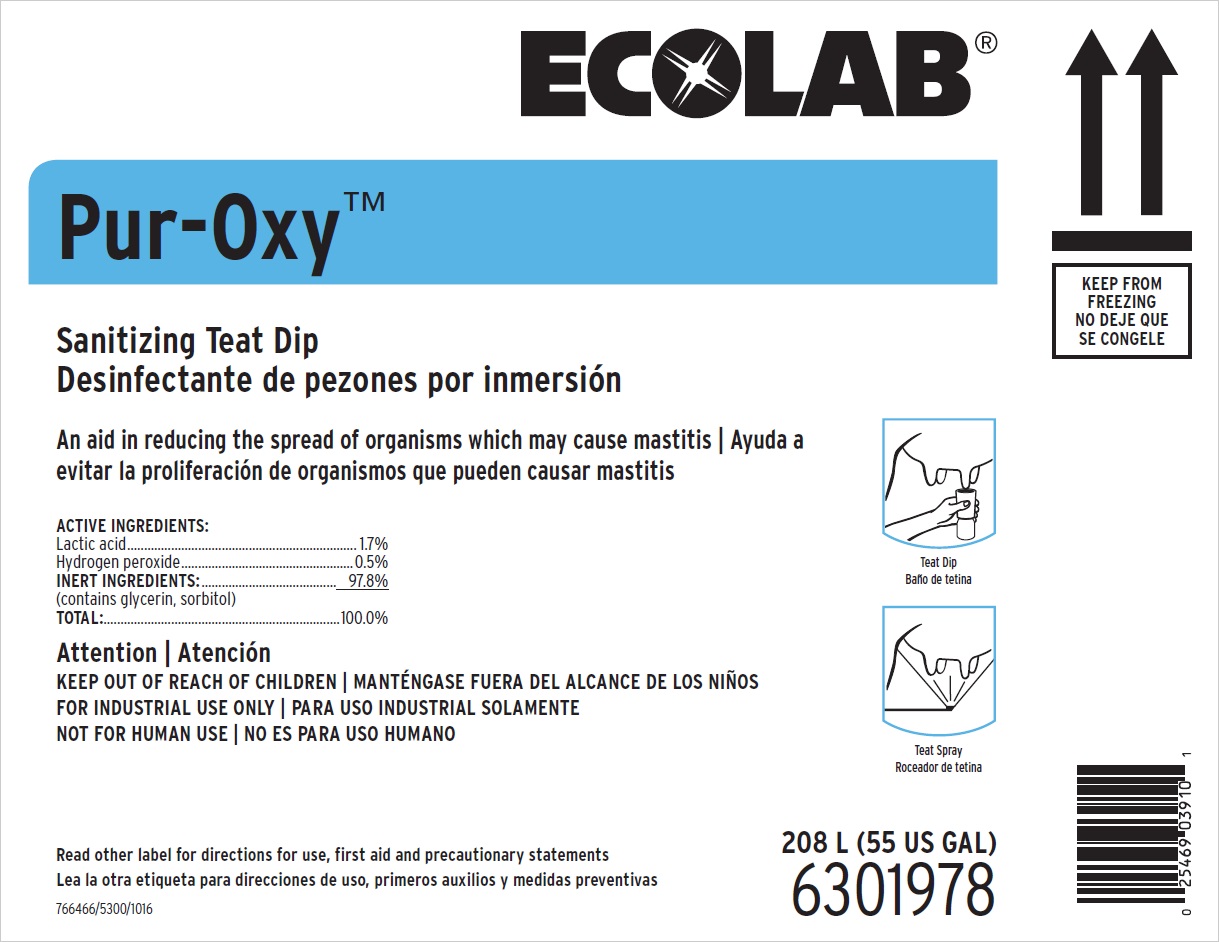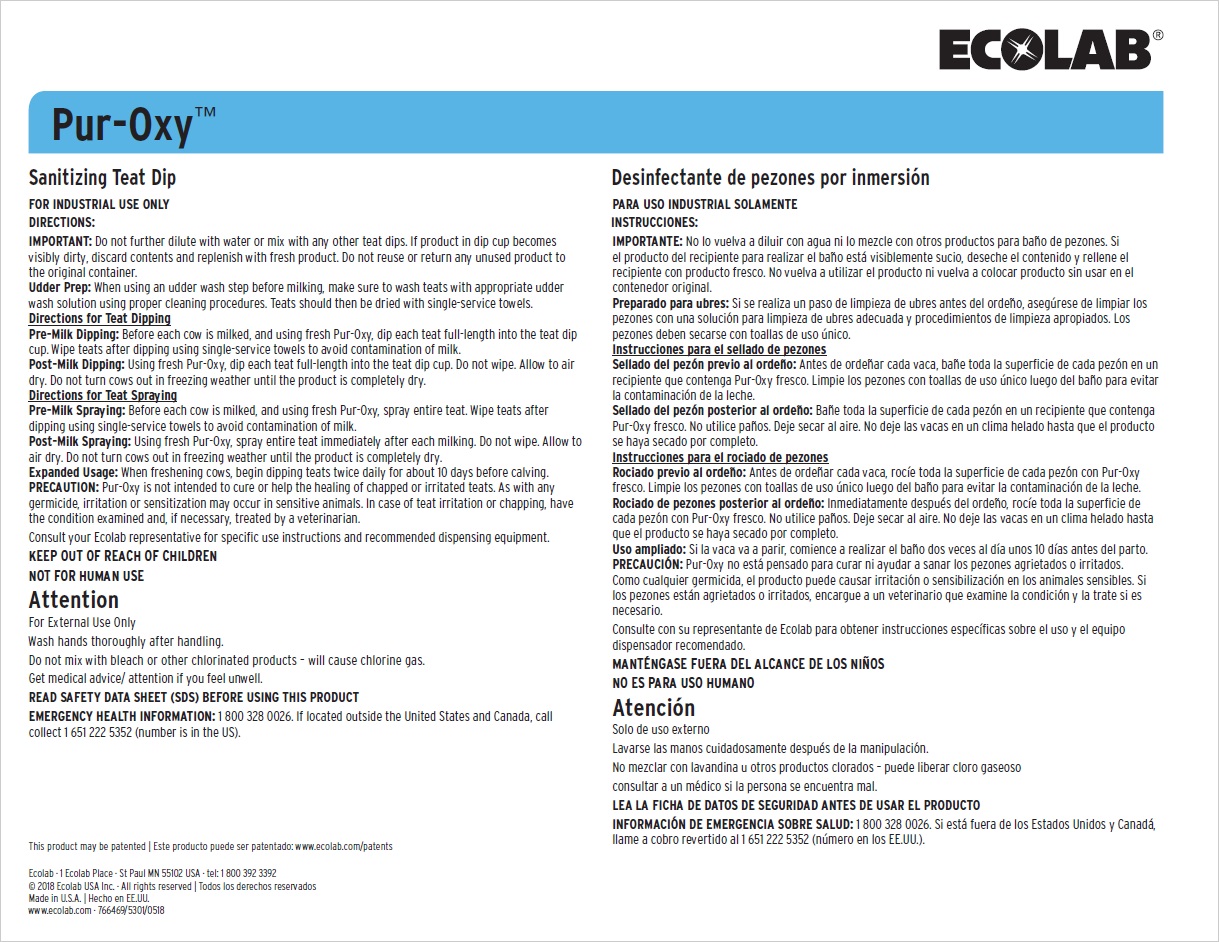 DRUG LABEL: Pur-Oxy
NDC: 47593-451 | Form: SOLUTION
Manufacturer: Ecolab Inc.
Category: animal | Type: OTC ANIMAL DRUG LABEL
Date: 20250827

ACTIVE INGREDIENTS: Lactic Acid 17 mg/1 mL; Hydrogen Peroxide 5 mg/1 mL
INACTIVE INGREDIENTS: GLYCERIN; SORBITOL

SAFE HANDLING WARNING

FOR INDUSTRIAL USE ONLY

KEEP OUT OF REACH OF CHILDREN

NOT FOR HUMAN USE

Attention

For External Use Only

Wash hands thoroughly after handling.

Do not mix with bleach or other chlorinated products – will cause chlorine gas.

Get medical advice/ attention if you feel unwell.

DIRECTIONS:

IMPORTANT: Do not further dilute with water or mix with any other teat dips. If product in dip cup becomes visibly dirty, discard contents and replenish with fresh product. Do not reuse or return any unused product to the original container.

Udder Prep: When using an udder wash step before milking, make sure to wash teats with appropriate udder wash solution using proper cleaning procedures. Teats should then be dried with single-service towels.

Directions for Teat Dipping

Pre-Milk Dipping: Before each cow is milked, and using fresh Pur-Oxy, dip each teat full-length into the teat dip cup. Wipe teats after dipping using single-service towels to avoid contamination of milk.

Post-Milk Dipping: Using fresh Pur-Oxy, dip each teat full-length into the teat dip cup. Do not wipe. Allow to air dry. Do not turn cows out in freezing weather until the product is completely dry.

Directions for Teat Spraying

Pre-Milk Spraying: Before each cow is milked, and using fresh Pur-Oxy, spray entire teat. Wipe teats after dipping using single-service towels to avoid contamination of milk.

Post-Milk Spraying: Using fresh Pur-Oxy, spray entire teat immediately after each milking. Do not wipe. Allow to air dry. Do not turn cows out in freezing weather until the product is completely dry.

Expanded Usage: When freshening cows, begin dipping teats twice daily for about 10 days before calving.

PRECAUTION: Pur-Oxy is not intended to cure or help the healing of chapped or irritated teats. As with any germicide, irritation or sensitization may occur in sensitive animals. In case of teat irritation or chapping, have the condition examined and, if necessary, treated by a veterinarian.

Consult your Ecolab representative for specific use instructions and recommended dispensing equipment.

OTHER SAFETY INFORMATION

READ SAFETY DATA SHEET (SDS) BEFORE USING THIS PRODUCT
EMERGENCY HEALTH INFORMATION: 1 800 328 0026. If located outside the United States and Canada, call collect 1 651 222 5352 (number is in the US).

PRINCIPAL DISPLAY PANEL/REPRESENTATIVE LABEL

Ecolab

Pur-Oxy™

Sanitizing Teat Dip

An Aid in Reducing the Spread of Organisms Which May Cause Mastitis

ACTIVE INGREDIENTS:
Lactic acid............................................................ 1.7%
Hydrogen peroxide................................................ 0.5%
INERT INGREDIENTS: ........................................ 97.8%
(contains glycerin, sorbitol)
TOTAL:...............................................................100.0%

208 L (55 US GAL)

6301978

Ecolab · 1 Ecolab Place · St Paul MN 55102 USA · tel: 1 800 392 3392

© 2018 Ecolab USA Inc. · All rights reserved

www.ecolab.com · 766469/5300/0518